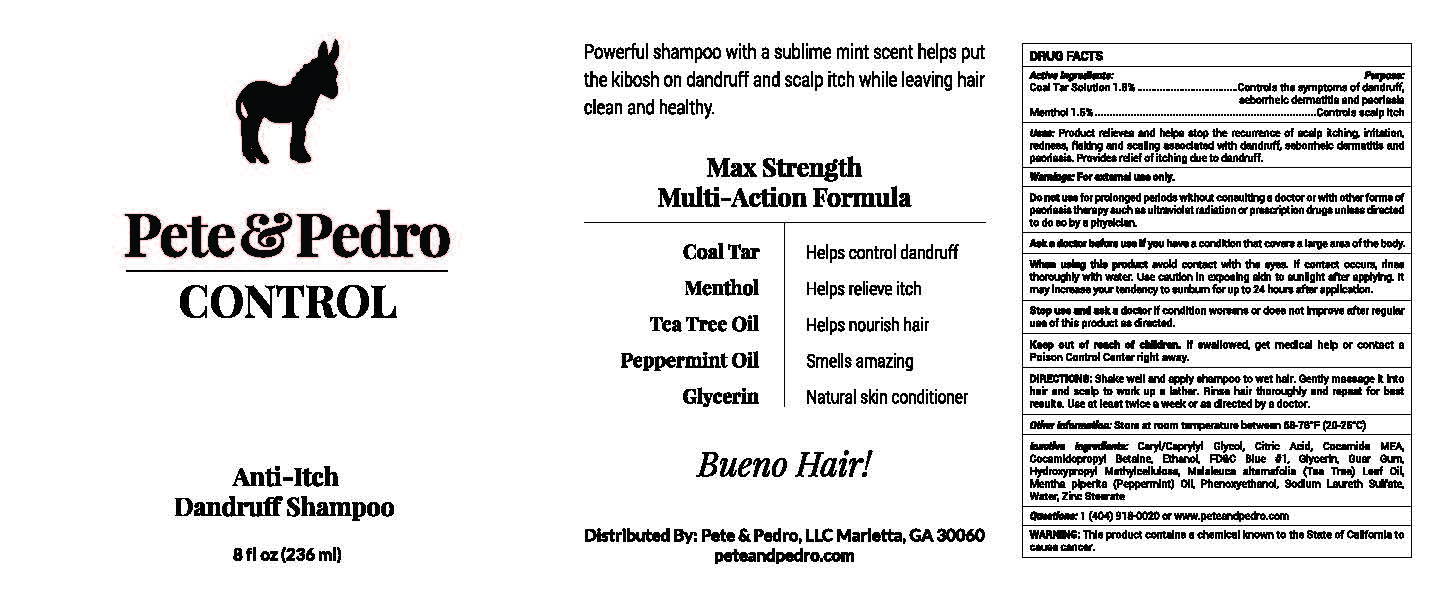 DRUG LABEL: Pete and Pedro
NDC: 52261-0900 | Form: LOTION/SHAMPOO
Manufacturer: Cosco International, Inc.
Category: otc | Type: HUMAN OTC DRUG LABEL
Date: 20190124

ACTIVE INGREDIENTS: COAL TAR 0.001836 kg/1 kg; MENTHOL 0.00153 kg/1 kg
INACTIVE INGREDIENTS: WATER; GUAR GUM; GLYCERIN; HYDROXYMETHYL CELLULOSE; COCAMIDOPROPYL BETAINE; COCO MONOETHANOLAMIDE; SODIUM LAURETH SULFATE; ZINC STEARATE; PEPPERMINT OIL; TEA TREE OIL; CITRIC ACID MONOHYDRATE; PHENOXYETHANOL; CAPRYLYL GLYCOL; FD&C BLUE NO. 1

Pete and Pedro Control Anti Itch Dandruff Shampoo

DRUG FACTS

Active Ingredients:

Coal Tar Solution 1.8%..................Controls the symptoms of dandruff, seborrheic dermatitis and psoriasis

Menthol 1.5%..............................Contols scalp itch

PURPOSE

Uses: Product relieves and helps stop the recurrence of scalp itching, irritation, redness, flaking and scaling associated with dandruff, seborrheic dermatitis and psoriasis. Provide relief of itching due to dandruff.

Warnings: For external use only.

Do not use for prolonged periods without consulting a doctor or with other forms of psoriasis therapy such as ultraviolet radiation or prescription drugs unless directed to do so by a physician.

Ask a doctor before use if you have a conditiion that covers a large area of the body.

When using this product avoid contact with the eyes. If contact occurs, rinse thoroughly with water. Use caution in exposing skin to sunlight after applying. It may increase you tendency to sunburn for up to 24 hours after application.

Stop use and ask doctor if condition worsens or does not improve after regular use of the product as directed.

Keep out of reach of children. If swallowed, get medical help or contact a Poison Control Center right away.

DOSAGE AND ADMINISTRATION

DIRECTIONS: Shake well and apply shampoo to wet hair. Gently massage it into hair and scalp to work up a lather. Rinse hair thoroughly and repeat for best results. Use at least twice a week or as directed by a doctor.

Other Information: Store at room temperature between 68-78

INACTIVE INGREDIENT

Inactive Ingredients: Caprylyl Glycol, Citric Acid, Cocamide MEA, Cocamidopropyl Betaine, Ethanol, FD&C Blue #1, Glycerin, Guar Gum, Hydroxypropyl Methylcellulose, Melaleuca Alternafolia (Tea Tree) Leaf Oil, Mentha Piperita (Peppermint) Oil, Phenoxyethanol, Sodium Laureth Sulfate, Water, Zinc Stearate

QUESTIONS

Questions: 1 (404) 918-0020 or www.peteandpedro.com

WARNINGS

WARNING: This product contains a chemical known to the State of California to cause cancer.